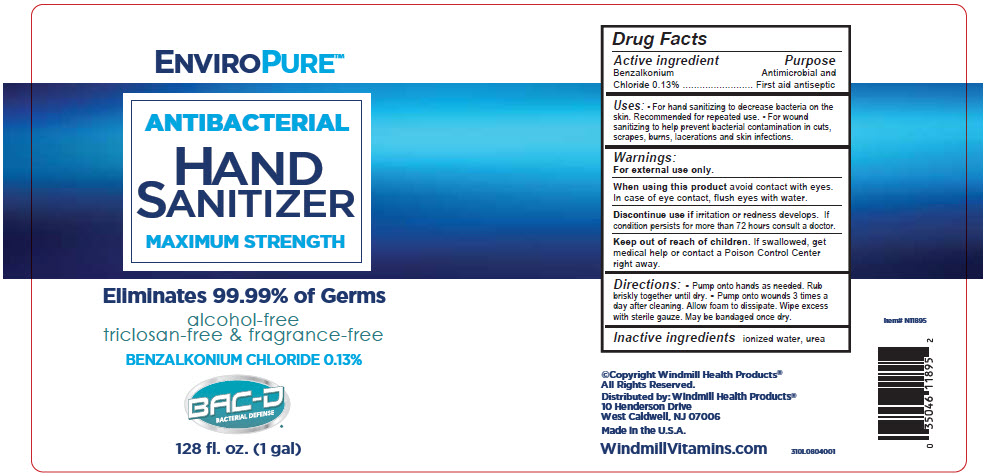 DRUG LABEL: EnviroPure Antibacterial Hand Sanitizer Maximum Strength (Alcohol-Free)
NDC: 74154-004 | Form: LIQUID
Manufacturer: Windmill Health Products, LLC
Category: otc | Type: HUMAN OTC DRUG LABEL
Date: 20220203

ACTIVE INGREDIENTS: Benzalkonium Chloride 0.13 mg/100 mL
INACTIVE INGREDIENTS: water; urea

EnviroPure™ Antibacterial Hand Sanitizer Maximum Strength (Alcohol-Free)

Drug Facts

Active ingredient

Benzalkonium Chloride 0.13%

Purpose

Antimicrobial and First aid antiseptic

Uses

- For hand sanitizing to decrease bacteria on the skin. Recommended for repeated use.
- For wound sanitizing to help prevent bacterial contamination in cuts, scrapes, burns, lacerations and skin infections.

Warnings

For external use only.

When using this product avoid contact with eyes. In case of eye contact, flush eyes with water.

STOP USE

Discontinue use if irritation or redness develops. If condition persists for more than 72 hours consult a doctor.

Keep out of reach of children. If swallowed, get medical help or contact a Poison Control Center right away.

Directions

- Pump onto hands as needed. Rub briskly together until dry.
- Pump onto wounds 3 times a day after cleaning. Allow foam to dissipate. Wipe excess with sterile gauze. May be bandaged once dry.

Inactive ingredients

ionized water, urea

Distributed by: Windmill Health Products®
10 Henderson Drive
West Caldwell, NJ 07006

PRINCIPAL DISPLAY PANEL - 1 gal Bottle Label

ENVIROPURE™

ANTIBACTERIAL

HAND
SANITIZER

MAXIMUM STRENGTH

Eliminates 99.99% of Germs

alcohol-free
triclosan-free & fragrance-free

BENZALKONIUM CHLORIDE 0.13%

BAC-D
BACTERIAL DEFENSE®

128 fl. oz. (1 gal)